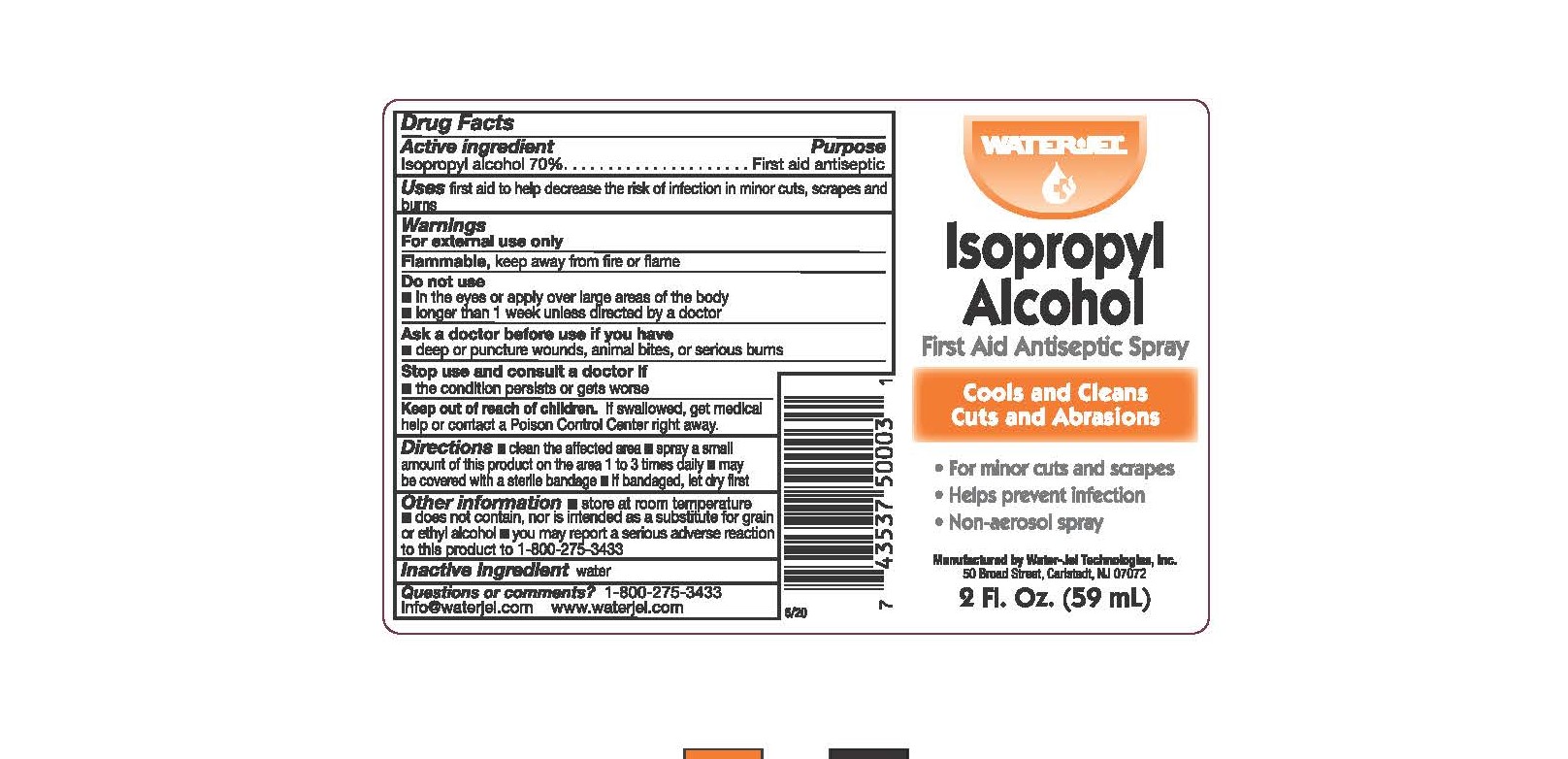 DRUG LABEL: Isopro First Aid
NDC: 59898-402 | Form: SPRAY
Manufacturer: Water-Jel Technologies
Category: otc | Type: HUMAN OTC DRUG LABEL
Date: 20250106

ACTIVE INGREDIENTS: ISOPROPYL ALCOHOL 70 mL/100 mL
INACTIVE INGREDIENTS: WATER

Isopropyl Alcohol Spray

Active ingredient

Isopropyl alcohol 70%

Purpose

First aid antiseptic

Uses

first aid to help decrease the risk of infection in minor cuts, scrapes and burns

WARNINGS

For external use only

Flammable

keep away from fire or flame

Do not use

- in the eyes or apply over large areas of the body
- longer than 1 week unless directed by a doctor

Ask a doctor before use if you have

deep or puncture wounds, animal bites, or serious burns

Stop use and consult a doctor if

- the condition persists or gets worse

Keep out of the reach of children

If swallowed, get medical help or contact a Poison Control Center right away.

Directions

- clean the affected area
- spray a small amount of this product in the area 1 to 3 times daily
- may be covered with a sterile bandage
- if bandaged, let dry first

Other information

- store at room temperature
- does not contain, nor is intended as a substitute for grain or ethyl alcohol
- you may report a serious adverse reaction to this product to 1-800-275-3433

Inactive ingredient

water

Questions or comments?

1-800-275-3433 info@waterjel.com www.waterjel.com
Manufactured by Water-Jel Technologies, Inc.

50 Broad Street, Carlstadt, NJ 07072